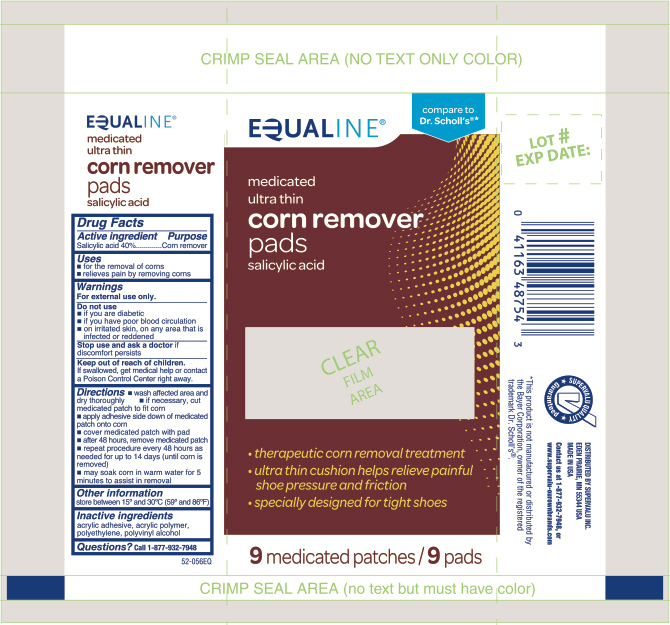 DRUG LABEL: Salicylic Acid
NDC: 41163-136 | Form: PATCH
Manufacturer: United Natural Foods, Inc. dba UNFI
Category: otc | Type: HUMAN OTC DRUG LABEL
Date: 20260102

ACTIVE INGREDIENTS: SALICYLIC ACID 40 mg/9 1
INACTIVE INGREDIENTS: POLYVINYL ALCOHOL; HIGH DENSITY POLYETHYLENE

Equaline Ultra Thin Corn Removers

Active ingredient

Salicylic acid 40%

Purpose

Corn remover

Use

- for the removal of corns
- relieves pain by removing corns

Warnings

For external use only.

Do not use

- if you are a diabetic
- if you have poor blood circulation
- on irritated skin, on any area that is infected or reddened

If discomfort persists

see your doctor or podiatrist

Keep out of reach of children.

If swallowed, get medical help or contact a Poison Control Center right away.

Directions

- wash affected area and dry area thoroughly
- if necessary, cut medicated patch to fit corn
- apply adhesive side down of medicated patch onto corn
- cover medicated patch with cover
- after 48 hours, remove medicated patch
- repeat procedure every 48 hours as needed for up to 14 days (until corn is removed)
- may soak corn in warm water for 5 minutes to assist in removal

Other information

store between 15°C to 30°C (59°F to 86°F)

Inactive ingredients

acrylic adhesive, acrylic polymer, polyethylene, polyvinyl alcohol

Questions?

1-866-964-0939

Principal Display Panel

Equaline

medicated
ultra thin
corn remover

pads

salicylic acid

- therapeutic corn removal treatment
- ultra thin cushion helps relieve painful shoe pressure and friction
- specifically designed for tight shoes

9 Medicated Patches/ 9 Pads